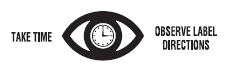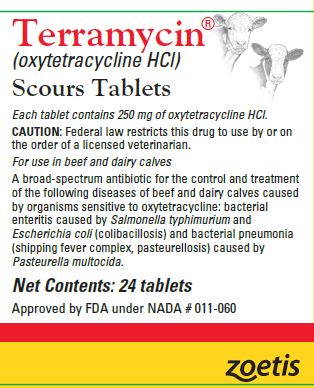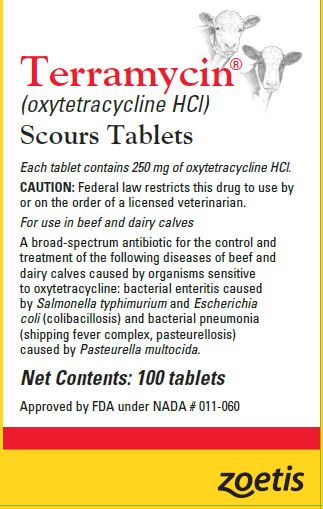 DRUG LABEL: Terramycin
NDC: 54771-1203 | Form: TABLET
Manufacturer: Zoetis Inc.
Category: animal | Type: PRESCRIPTION ANIMAL DRUG LABEL
Date: 20230608

ACTIVE INGREDIENTS: OXYTETRACYCLINE HYDROCHLORIDE 250 mg/1 1

Terramycin® Scours Tablets

Terramycin®
(oxytetracycline HCl)
Scours Tablets
Each tablet contains 250 mg of oxytetracycline HCl.
CAUTION: Federal law restricts this drug to use by or on the order of a licensed veterinarian.
A broad-spectrum antibiotic for use in beef and dairy calves
Read Entire Package Outsert Carefully Before Using This Product

DESCRIPTION

Terramycin Scours Tablets is an oral formulation containing oxytetracycline, a versatile, broad-spectrum antibiotic that possesses potent antimicrobial activity, for use in beef and dairy calves.

INDICATIONS AND USAGE

Terramycin Scours Tablets are recommended for oral administration for the control and treatment of the following diseases in beef and dairy calves caused by organisms sensitive to oxytetracycline: bacterial enteritis caused by Salmonella typhimurium and Escherichia coli (colibacillosis) and bacterial pneumonia (shipping fever complex, pasteurellosis) caused by Pasteurella multocida.

WARNINGS

Discontinue treatment at least 7 days prior to slaughter. Not for use in lactating dairy cattle. A withdrawal period has not been established for this product in preruminating calves. Do not use in calves to be processed for veal.

PRECAUTIONS

Exceeding the recommended dosage level of 2 tablets per 100 lb of body weight every 12 hours (10 mg/lb of body weight daily), or administering at this recommended level for more than 4 consecutive days, may result in antibiotic residues beyond the withdrawal time.

Organisms may vary in their degree of susceptibility to any chemotherapy. If no improvement is observed after recommended treatment, diagnosis and susceptibility should be reexamined.

Rarely do side reactions or allergic manifestations occur in calves treated with Terramycin. If any unusual reactions are noted, discontinue use of the drug immediately and call a veterinarian.

Since bacteriostatic drugs may interfere with the bacterial action of penicillin, it is advisable to avoid giving Terramycin in conjunction with penicillin.

DOSAGE AND ADMINISTRATION

For control of bacterial enteritis and bacterial pneumonia orally administer 1 tablet per 100 lb of body weight every 12 hours (5 mg/ lb of body weight daily in divided doses) for up to 4 consecutive days.

For treatment of bacterial enteritis and bacterial pneumonia orally administer 2 tablets per 100 lb of body weight every 12 hours (10 mg/lb of body weight daily in divided doses) for up to 4 consecutive days.

Dosage should continue until the animal returns to normal and for 24–48 hours after symptoms have subsided. Treatment should not exceed 4 consecutive days.

Care of Sick Animals

The use of antibiotics in the management of disease is based on an accurate diagnosis and an adequate course of treatment. When properly used in the treatment of diseases caused by oxytetracycline-susceptible organisms, most animals treated with Terramycin Scours Tablets show a noticeable improvement within 24–48 hours. If improvement does not occur within this period of time, the diagnosis and course of treatment should be reevaluated. It is recommended that the diagnosis and treatment of animal diseases be carried out by a veterinarian. Since many diseases look alike but require different types of treatment, the use of professional veterinary and laboratory services can reduce treatment time, costs, and needless losses. Good housing, sanitation, and nutrition are important in the maintenance of healthy animals and are essential in the treatment of disease.

RECOMMENDED STORAGE

Store below 25°C (77°F).

For Animal Use Only

Not For Human Use

Approved by FDA under NADA # 011-060

zoetis

Distributed by:
Zoetis Inc.
Kalamazoo, MI 49007
Product of China
40039318
Revised: June 2022

PRINCIPAL DISPLAY PANEL - 24 Tablet Bottle Label

40039319

PRINCIPAL DISPLAY PANEL - 100 Tablet Bottle Label

40039320